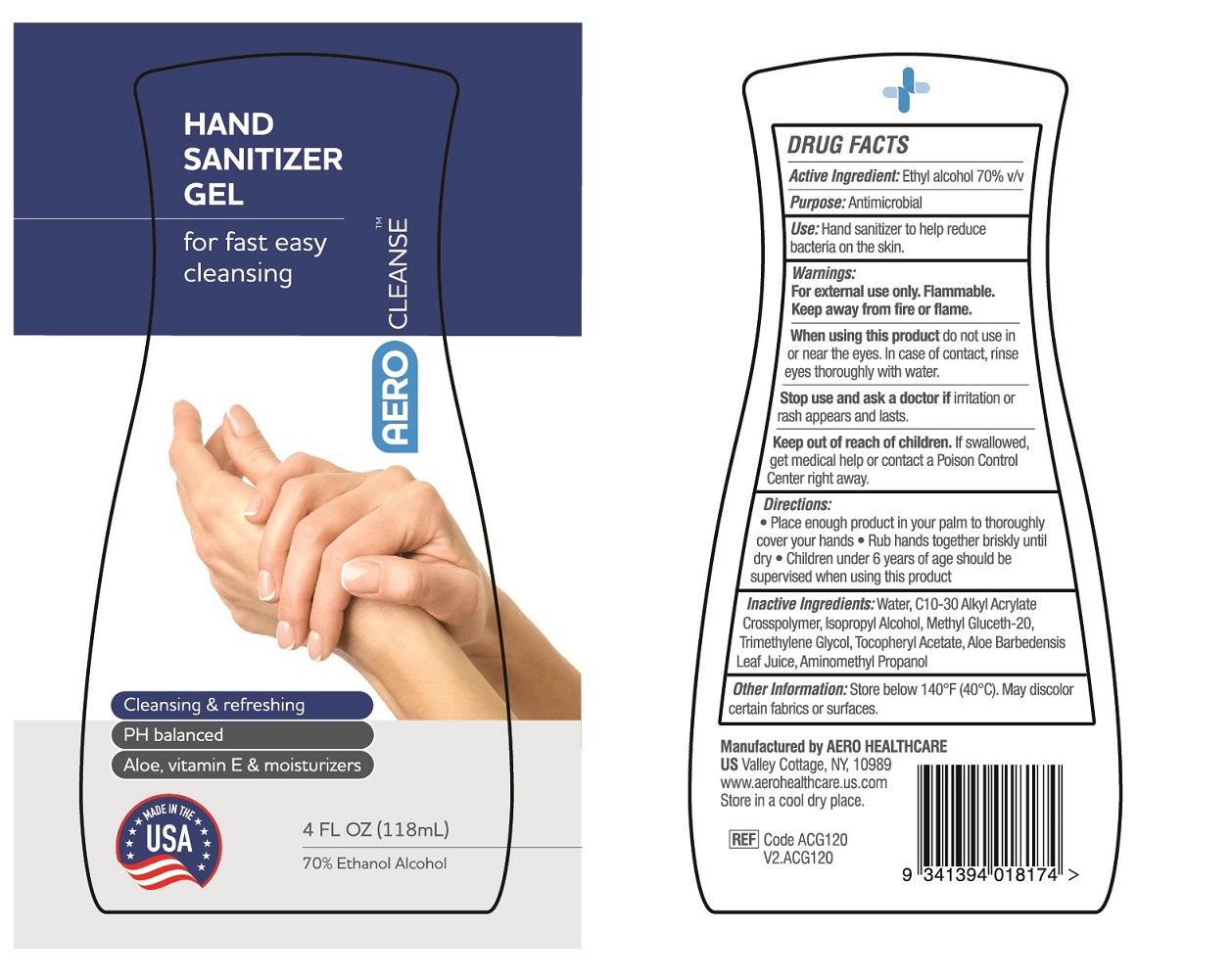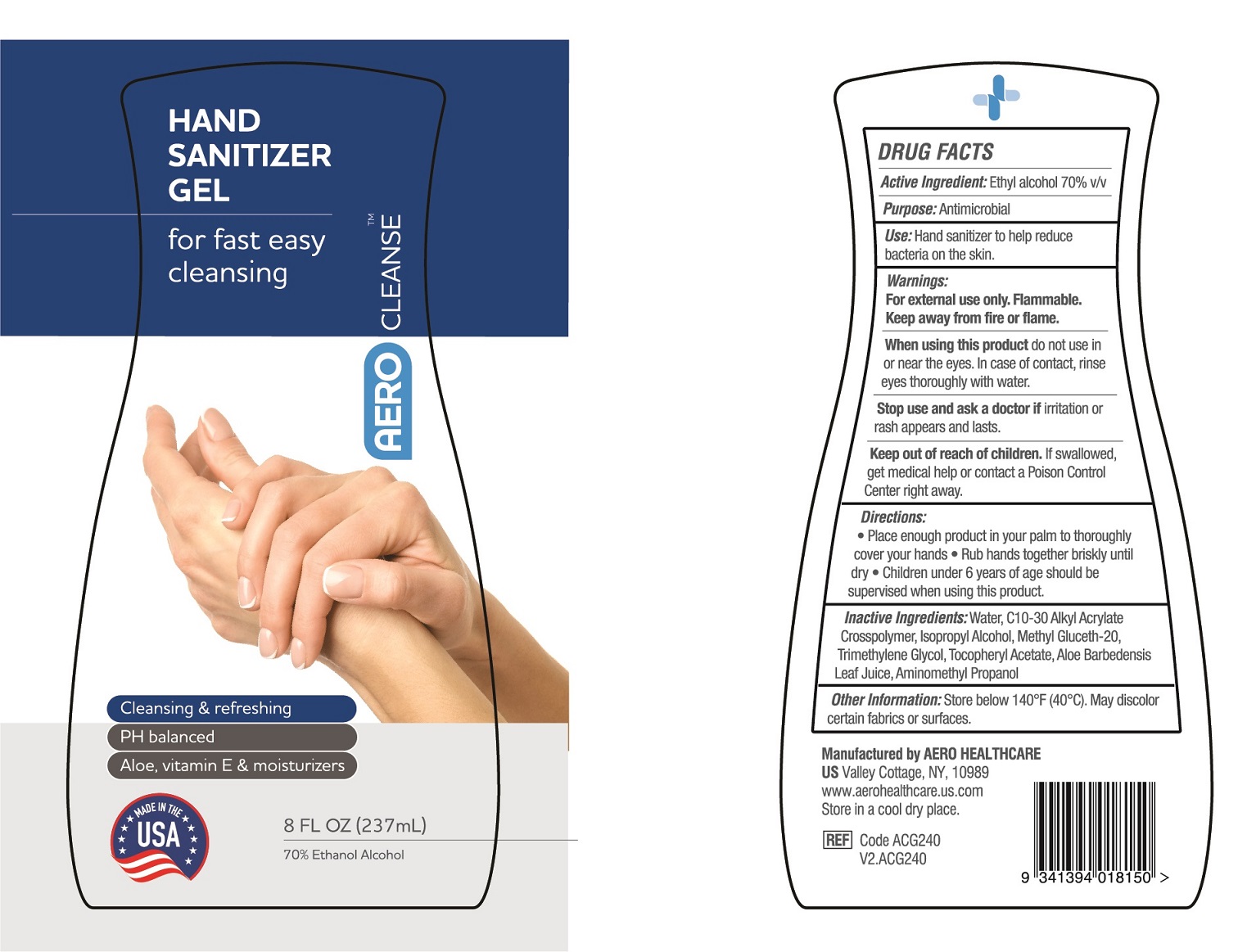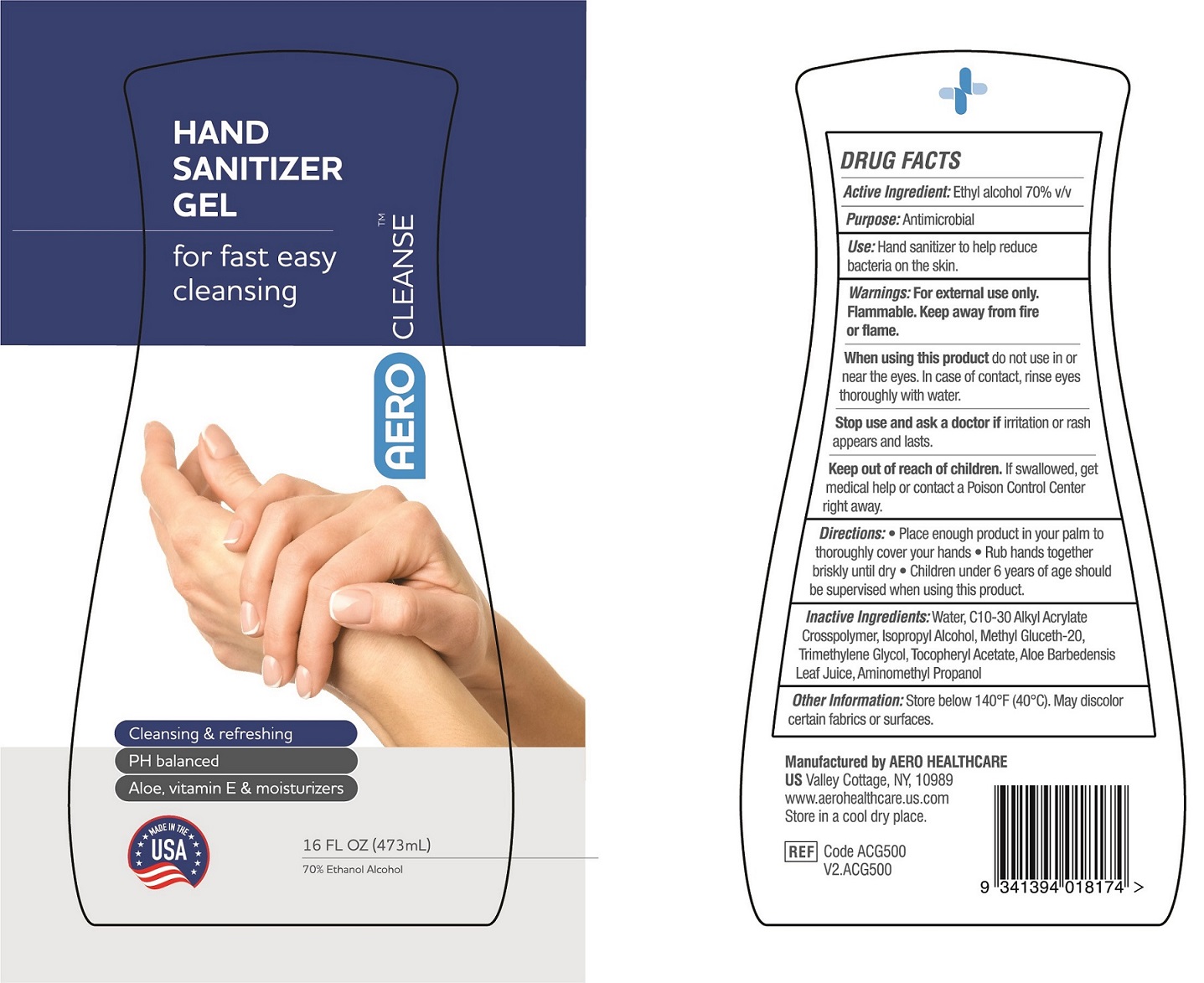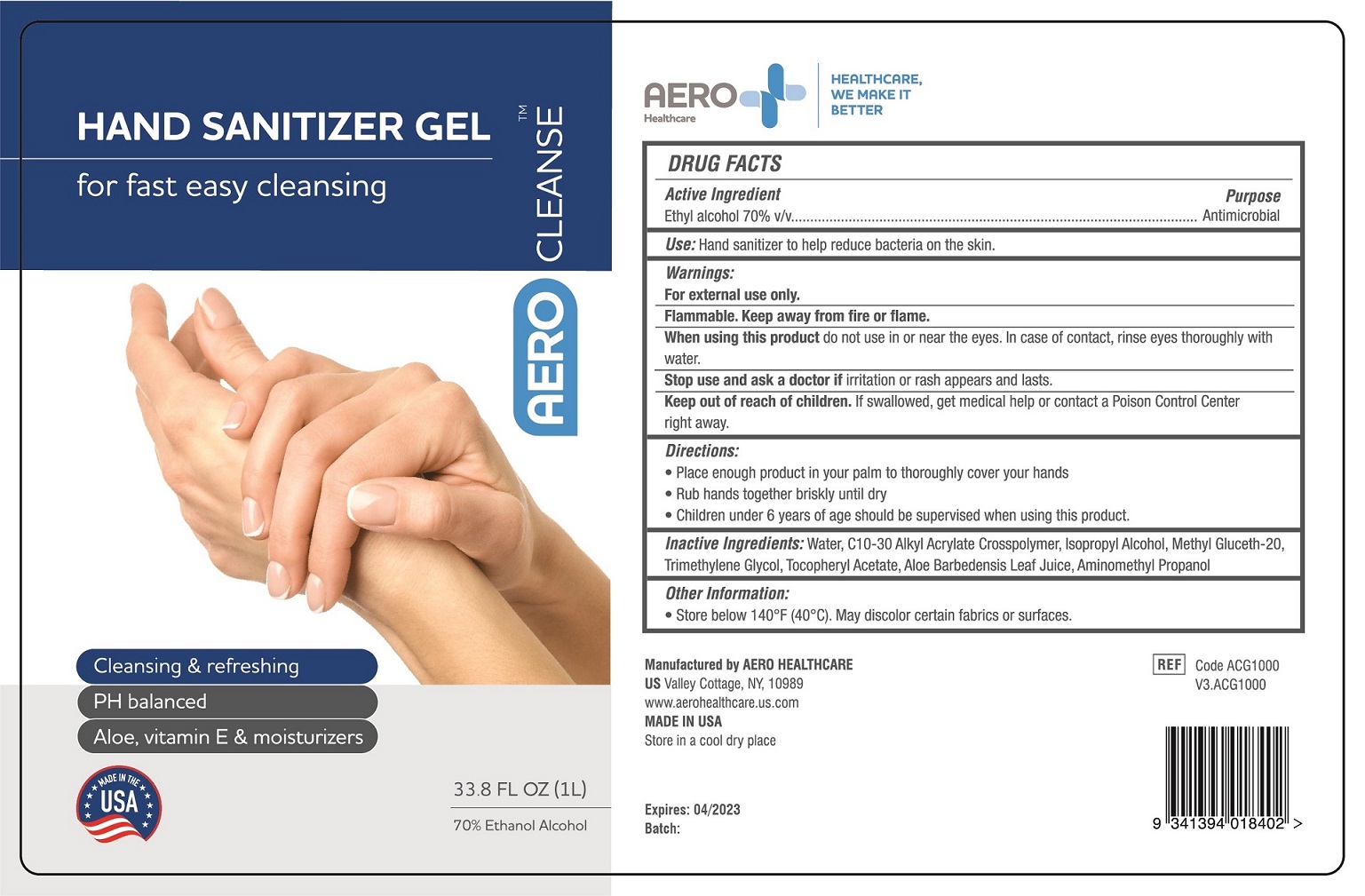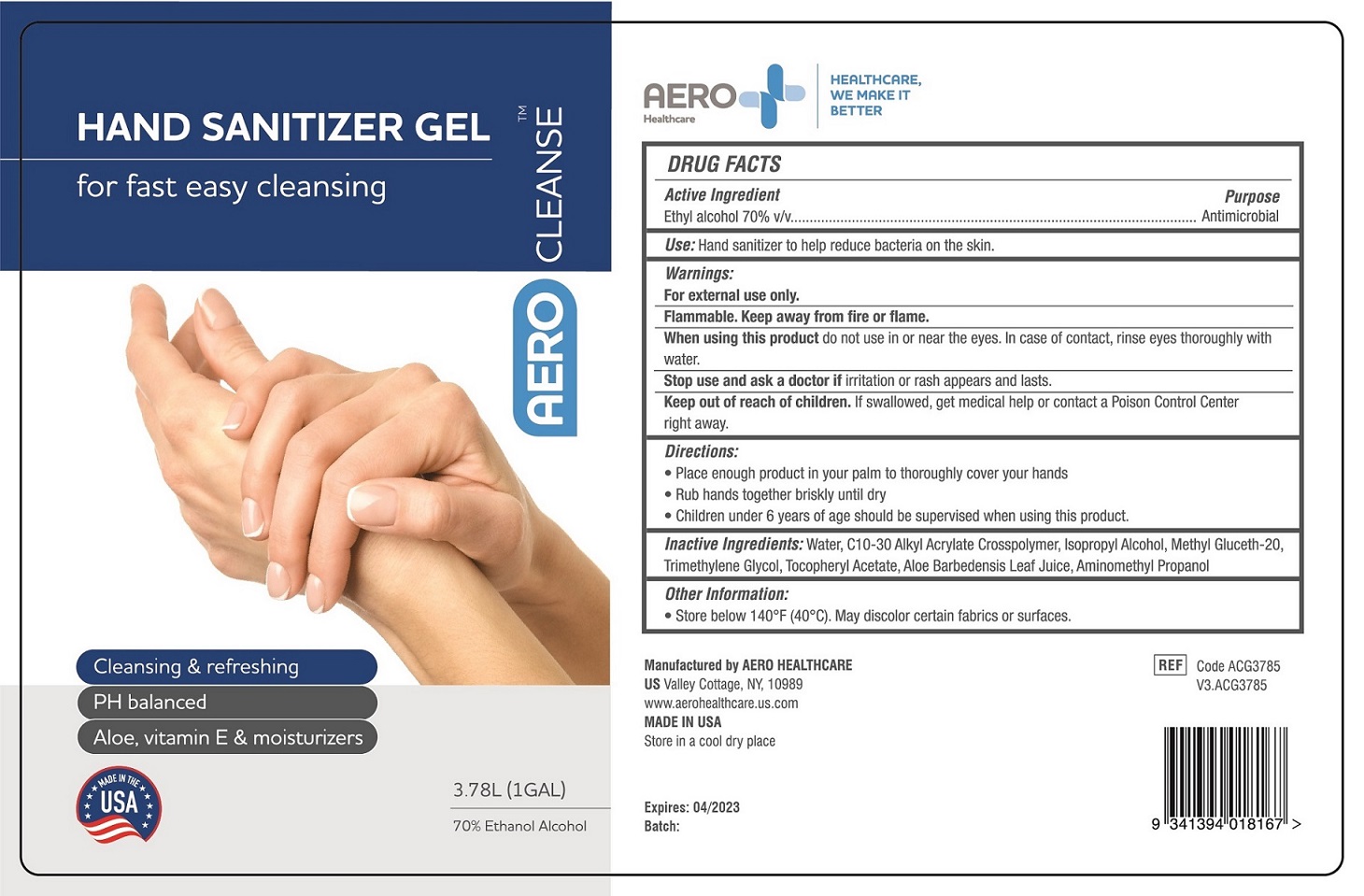 DRUG LABEL: AeroCleanse Hand Sanitizer
NDC: 55305-131 | Form: GEL
Manufacturer: Aero Healthcare US LLC
Category: otc | Type: HUMAN OTC DRUG LABEL
Date: 20220331

ACTIVE INGREDIENTS: ALCOHOL 0.7 mL/1 mL
INACTIVE INGREDIENTS: PROPANEDIOL; WATER; CARBOMER INTERPOLYMER TYPE A (ALLYL SUCROSE CROSSLINKED); .ALPHA.-TOCOPHEROL ACETATE; ALOE VERA LEAF; AMINOMETHYLPROPANOL; ISOPROPYL ALCOHOL; METHYL GLUCETH-20

AeroCleanse Hand Sanitizer Gel

Active Ingredient

Ethyl alcohol 70% v/v

Purpose

Antimicrobial

Use

Hand sanitizer to help reduce bacteria on the skin

Warnings

Flammable. Keep away from fire or flame.

For external use only

When using this product do not use in or near the eyes. In case of contact, rinse eyes thoroughly with water.

Stop use and ask a doctor if irritation or rash appears and lasts

Keep out of reach of children. If swallowed, get medical help or contact a Poison Control Center right away.

Directions

- Place enough product in your palm to thoroughly cover your hands
- Rub hands together briskly until dry
- Children under 6 years of age should be supervised when using this product.

Inactive Ingredients

Water, Acrylates Copolymer, Trimethylene Glycol, Aloe Barbadensis Leaf Juice, Tocopheryl Acetate, Triethanolamine

Other Information

- Store below 104°F (40°C)
- May discolor certain fabrics or surfaces